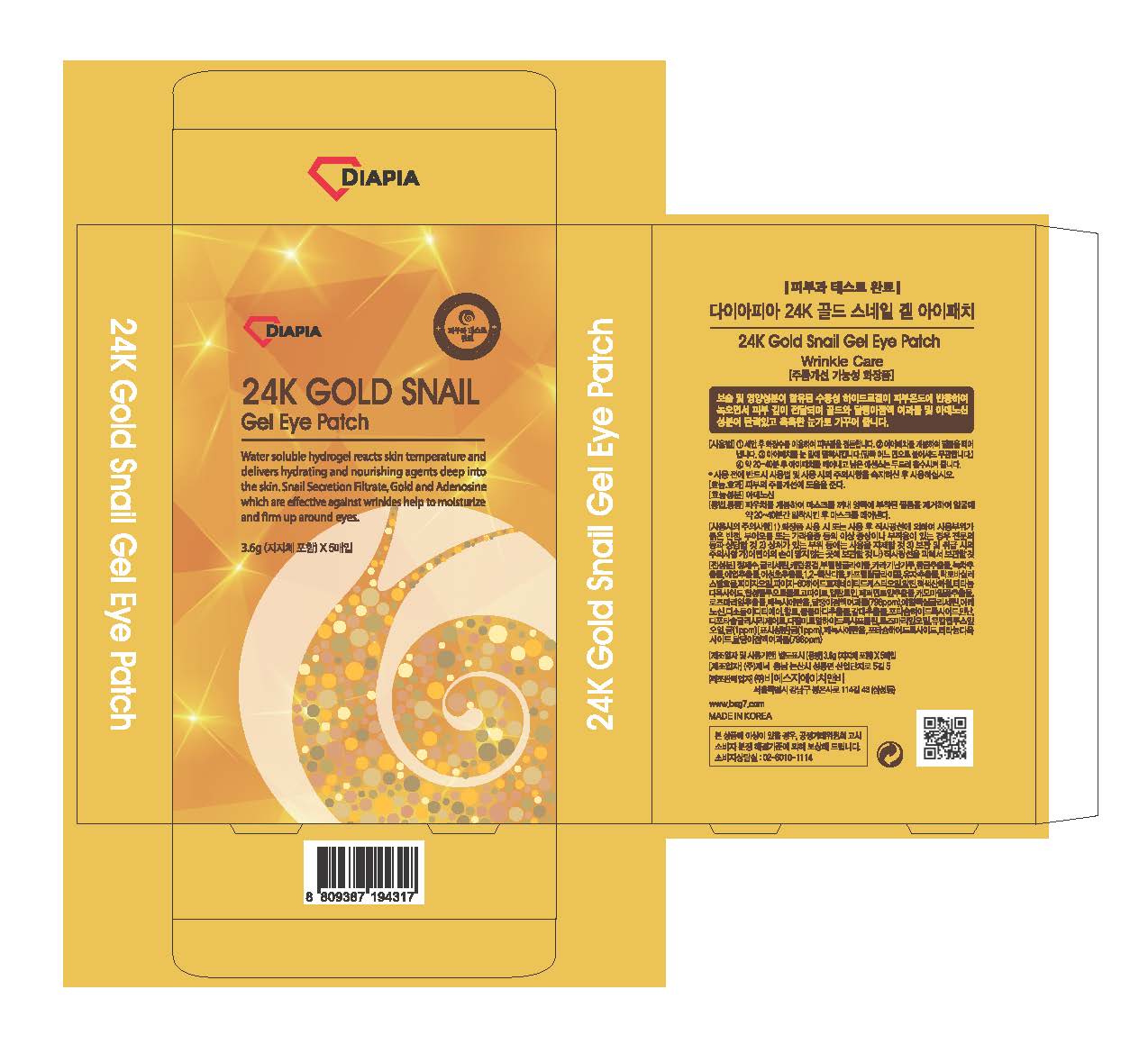 DRUG LABEL: DIAPIA 24K Gold SnailGel Eye Patch
NDC: 71857-0005 | Form: LIQUID
Manufacturer: BSG H & B Co., Ltd.
Category: otc | Type: HUMAN OTC DRUG LABEL
Date: 20171114

ACTIVE INGREDIENTS: GLYCERIN 20 g/100 g
INACTIVE INGREDIENTS: BUTYLENE GLYCOL; ALLANTOIN; WATER

ACTIVE INGREDIENT

glycerin

PURPOSE

wrinkle care

Keep out of reach of children

INDICATIONS AND USAGE

After cleansing face, apply mask onto face and remove after 20~40min

Keep out of reach of children.
Store in a cool, dry place and avoid direct sunlight.
Use immediately after opening

INACTIVE INGREDIENT

water butylene glycol, algin, allantoin, etc

DOSAGE AND ADMINISTRATION

for external use only